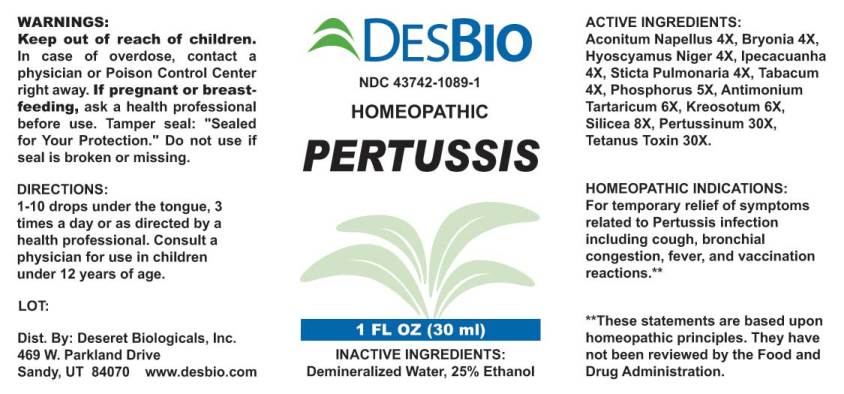 DRUG LABEL: Pertussis
NDC: 43742-1089 | Form: LIQUID
Manufacturer: Deseret Biologicals, Inc.
Category: homeopathic | Type: HUMAN OTC DRUG LABEL
Date: 20171031

ACTIVE INGREDIENTS: ACONITUM NAPELLUS 4 [hp_X]/1 mL; BRYONIA ALBA ROOT 4 [hp_X]/1 mL; HYOSCYAMUS NIGER 4 [hp_X]/1 mL; IPECAC 4 [hp_X]/1 mL; LOBARIA PULMONARIA 4 [hp_X]/1 mL; TOBACCO LEAF 4 [hp_X]/1 mL; PHOSPHORUS 5 [hp_X]/1 mL; ANTIMONY POTASSIUM TARTRATE 6 [hp_X]/1 mL; WOOD CREOSOTE 6 [hp_X]/1 mL; SILICON DIOXIDE 8 [hp_X]/1 mL; HUMAN SPUTUM, BORDETELLA PERTUSSIS INFECTED 30 [hp_X]/1 mL; CLOSTRIDIUM TETANI 30 [hp_X]/1 mL
INACTIVE INGREDIENTS: WATER; ALCOHOL

Drug Facts:

ACTIVE INGREDIENTS:

Aconitum Napellus 4X, Bryonia (Alba) 4X, Hyoscyamus Niger 4X, Ipecacuanha 4X, Sticta Pulmonaria 4X, Tabacum 4X, Phosphorus 5X, Antimonium Tartaricum 6X, Kreosotum 6X, Silicea 8X, Pertussinum 30X, Tetanus Toxin 30X.

HOMEOPATHIC INDICATIONS:

For temporary relief of symptoms related to Pertussis infection including cough, bronchial congestion, fever, and vaccination
reactions.**

**These statements are based upon homeopathic principles. They have not been reviewed by the Food and Drug Administration.

WARNINGS:

Keep out of reach of children. In case of overdose, contact a physician or Poison Control Center right away.

If pregnant or breast-feeding, ask a health professional before use.

Tamper seal: "Sealed for Your Protection."

Do not use if seal is broken or missing.

Keep out of reach of children. In case of overdose, contact a physician or Poison Control Center right away.

DIRECTIONS:

1-10 drops under the tongue, 3 times a day or as directed by a health professional. Consult a physician for use in children under 12 years of age.

HOMEOPATHIC INDICATIONS:

For temporary relief of symptoms related to Pertussis infection including cough, bronchial congestion, fever, and vaccination
reactions.**

**These statements are based upon homeopathic principles. They have not been reviewed by the Food and Drug Administration.

INACTIVE INGREDIENTS:

Demineralized Water, 25% Ethanol.

QUESTIONS:

Dist. By: Deseret Biologicals, Inc.
469 W. Parkland Drive
Sandy, UT 84070 www.desbio.com

PACKAGE LABEL DISPLAY:

DESBIO
NDC 43742-1089-1
HOMEOPATHIC
PERTUSSIS
1 FL OZ (30 ml)